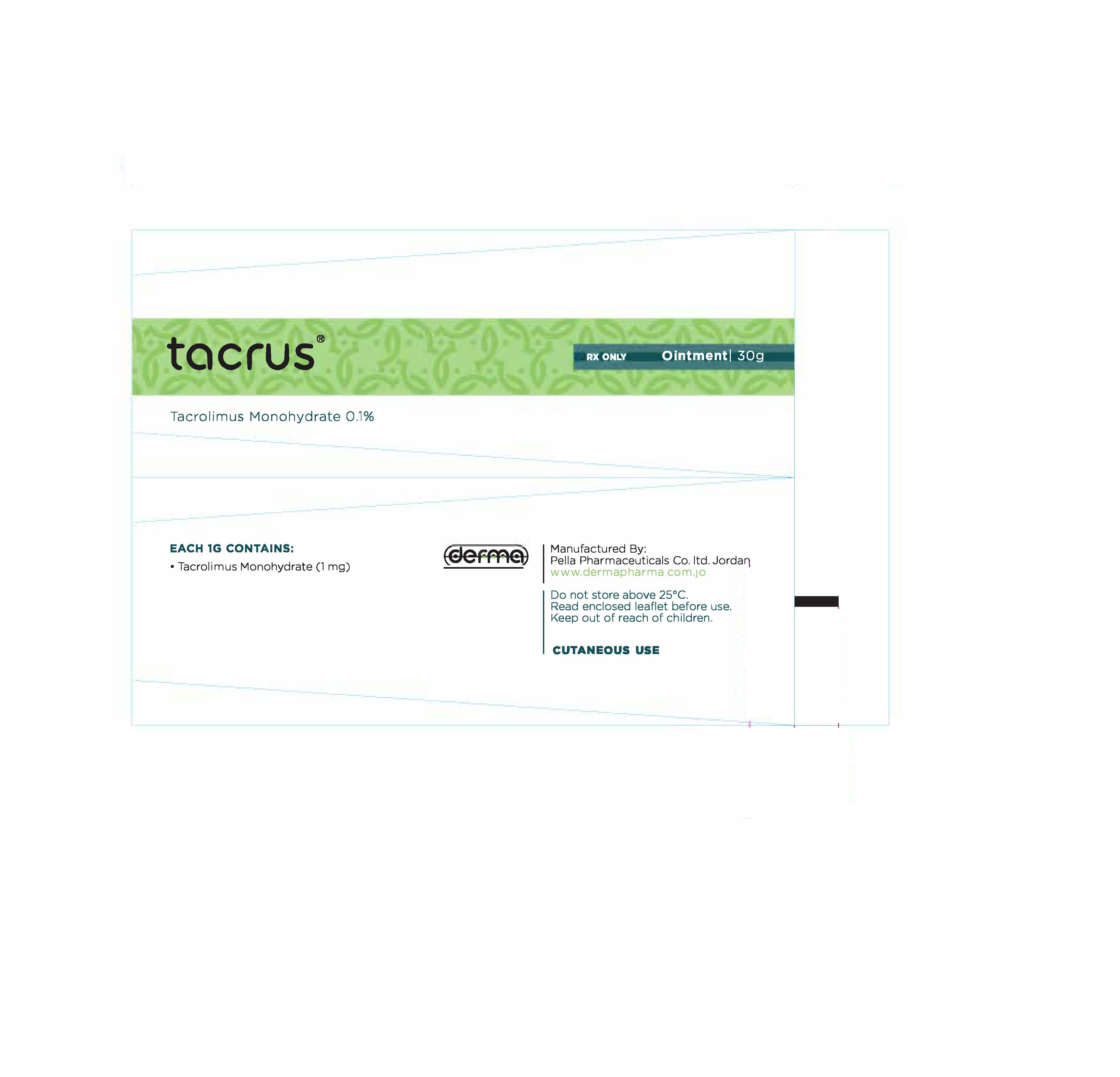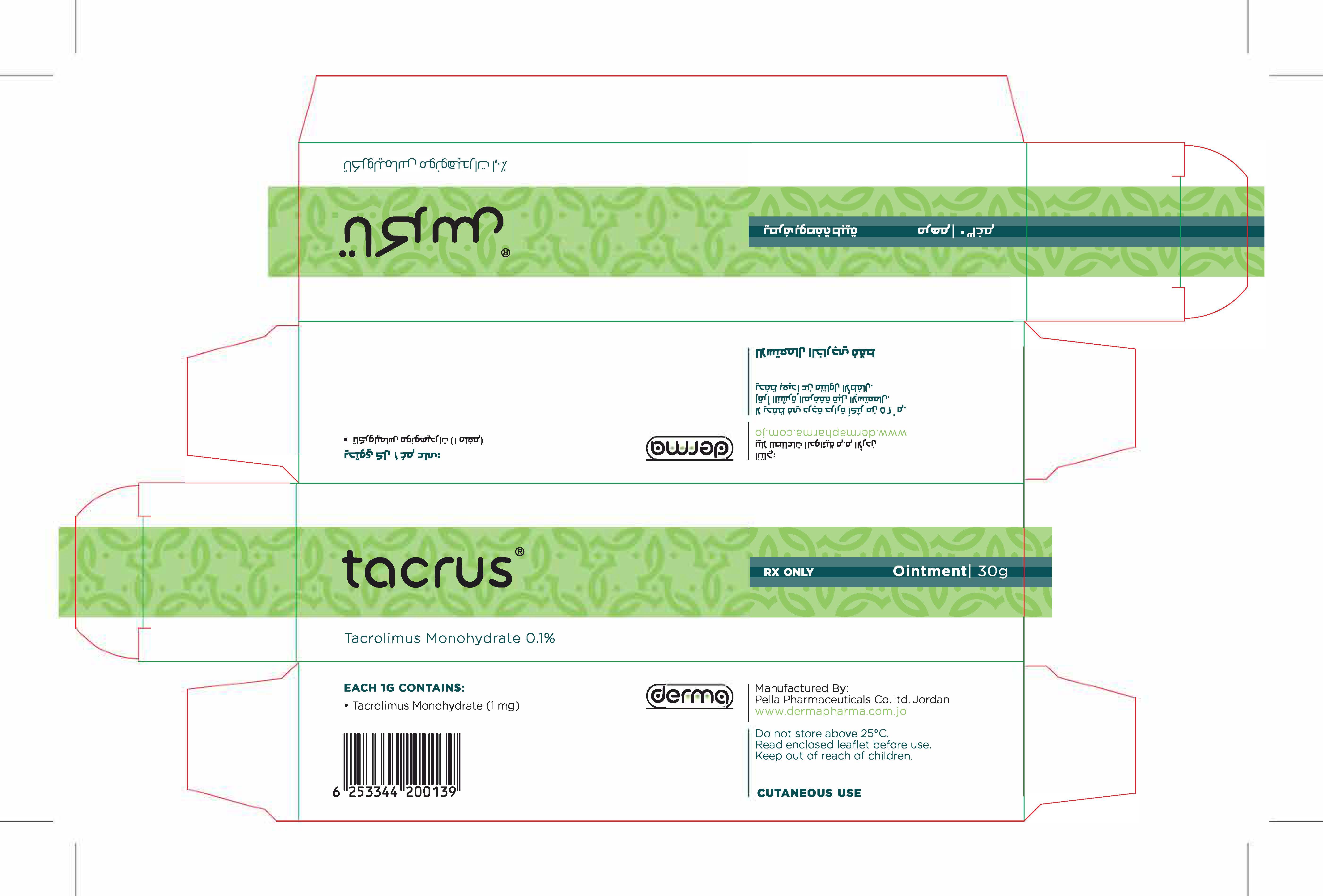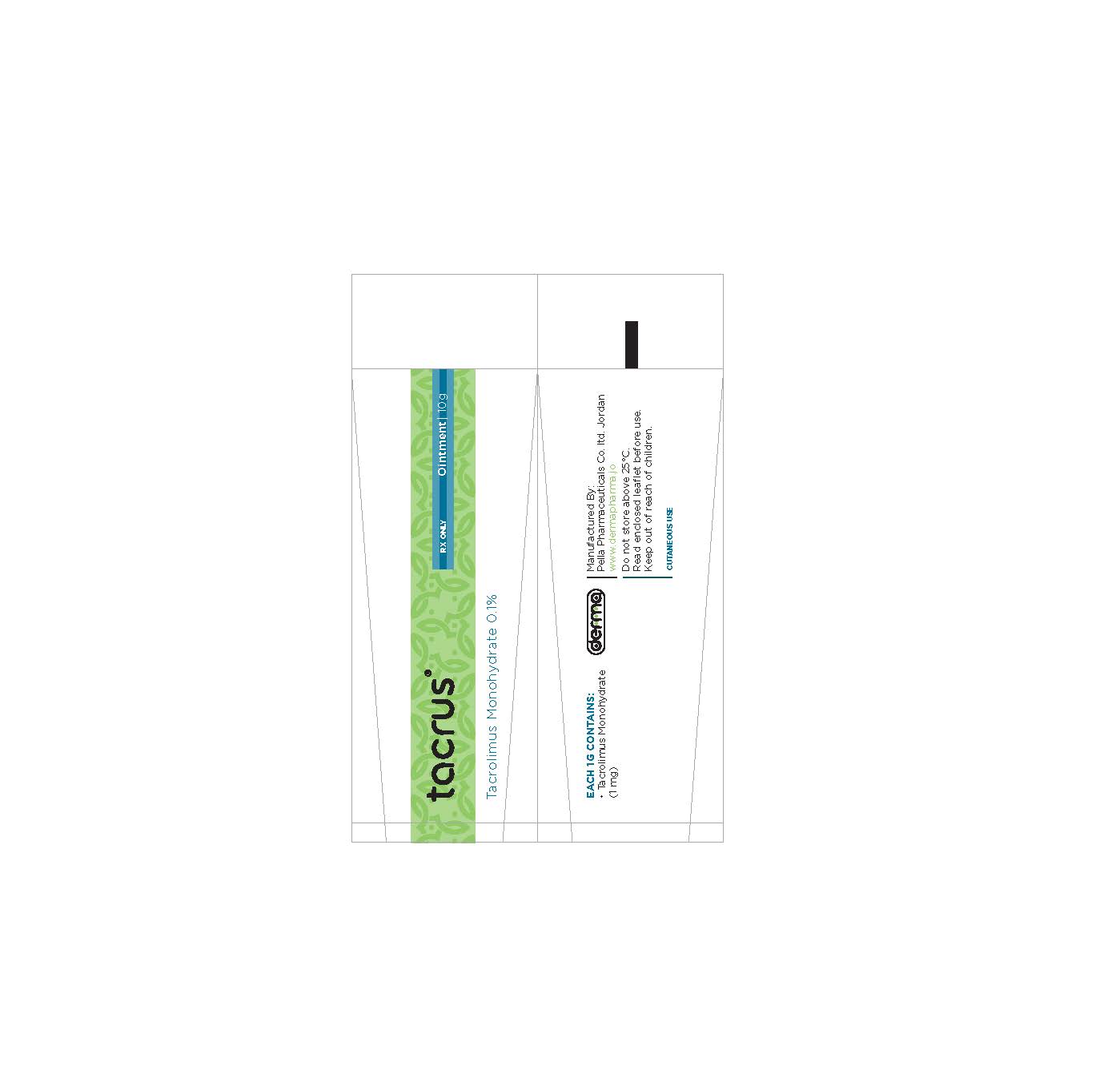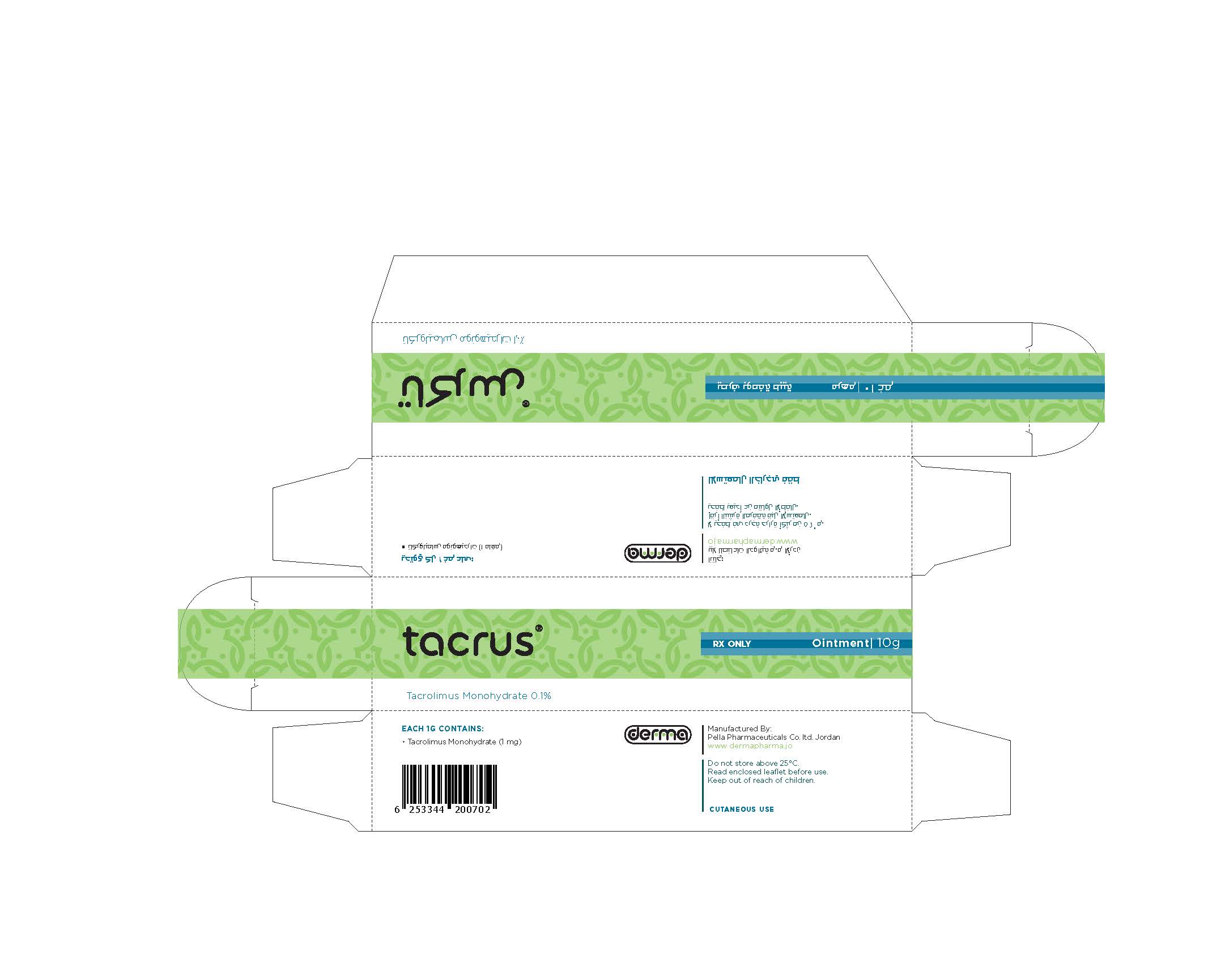 DRUG LABEL: Tacrus
NDC: 82160-124 | Form: OINTMENT
Manufacturer: Pella Pharmaceuticals Co. Ltd
Category: prescription | Type: HUMAN PRESCRIPTION DRUG LABEL
Date: 20241231

ACTIVE INGREDIENTS: TACROLIMUS 30 mg/30 g

Tacrus

Composition

Tacrus 0.1%
Each1 g contains: Tacrolimus 1 mg.
Excipients: Soft Paraffin, Mineral Oil, Propylene Carbonate, Hard Paraffin and White Beeswax

Indications

The active substance of Tacrus®, tacrolimus monohydrate, is an immune-modulating agent.
Tacrus® 0.03% ointment is used to treat moderate to severe atopic dermatitis (eczema) in adults who are not adequately responsive to or are intolerant of conventional therapies such as topical corticosteroids and in children (2 years of age and older) who failed to respond adequately to conventional therapies such as topical corticosteroids. Tacrus® 0.1 % ointment is used to treat moderate to severe atopic dermatitis (eczema) in adults who are not adequately responsive to or are intolerant of conventional therapies such as topical corticosteroids.
Once moderate to severe atopic dermatitis is cleared or almost cleared after up to 6 weeks treatment of a flare, and if you are experiencing frequent flares (i.e. 4 oc more per year), it may be possible to prevent flares coming back or prolong the time you are free from flares by using Tacrus® 0.1% ointment twice weekly.
In atopic dermatitis, an over-reaction of the skin's immune system causes skin inflammation (itchiness, redness, dryness).
Tacrus® alters the abnormal immune response and relieves the skin inflammation and the itch.

Contraindications

If you are allergic (hypersensitive) to tacrolimus or any of other ingredients of Tacrus or to macrolide anttbiotics (e.g. azithromycin, clarithromycin, erythromycin).

- Tacrolimus 0.03% is not approved in children younger than 2 years of age. Therefore it should not be used in this age group. Please consult your doctor.
- Tacms® 0.1 % ointment is not approved for children younger than 16 years of age. Therefore it should not be used in this age group. Please consult your doctor.
- The effect of treatment with Tacrolimus on the developing immune system in children, especially the young, has not been established.
- The safety of using Tacrus® for a long time is not known. A very small number of people who have used Tacrolimous ointment have had malignancies (for example skin or lymphoma) however a link to Tacrolimus ointment treatmert has not been shown.
- Avoid exposing the skin to long periods of sunlight or artificial sunlight such as tanning beds. If you spend time outdoors after applying Tacrus® use sunscreen and wear loose fitting clothing that protects the skin from the sun. In addition, ask your doctor for advice on other appropriate sun protection methods. If you are prescribed light therapy, inform your doctor that you are using Tacrus® as it is not recommended to use Tacrolimus and light therapy at the same time.
- If your doctor tells you to use Tacrus® twice weekly to keep your atopic dermatitis cleared, your condition should be reviewed by your doctor at least every 12 months, even if it remains under control. In children, maintenance treatment should be suspended after 12 months, to assess whether the need for continued treatment still exists.

Precautions while taking Tacrus®

Tell your doctor if you:

- Have liver failuer.
- Have any skin malignancies (tumors) or if you have a weakened immnne system (immuno-compromised) whatever the cause.
- Have inherited skin barrier disease such as Netherton's syndrome, lamellar ichthyosis (extensive scaling of the skin due to a thickening of the outer layer of the skin), or if you suffer from generalized erythroderma (inflammatory reddening and scalling of the entire skin).
- A cutaneous Graft Versus Host Disease (an immune reaction of the skin which is a common complication in patients who have undergone a bone marrowtransplant).
- Have swollen lymph nodes at initiation of treatment. If your lymph nodes become swollen during treatment with Tacrus®, consult your doctor.
- Have infected lesions. Do not apply the ointment to infected lesions.
- Notice any change to the appearance of your skin, please inform your physician.

Lactation

Don't use Tacrus® if you are breast-feeding.
Ask your doctor or pharmacist before taking any medicine.

Pregnancy

Don't use Tacrus® if you are pregnant.
Ask your doctor or pharmcist before taking any medicine.

Drug Interactions

Please tell your doctor or pharmacist if you are taking or have recently taken any other medicines, including medicines obtained without a prescription.
You may use moisturizing creams and lotions during treatment with Tacrus® but these products should not be used within two hours of applying Tacrus®.
The use of Tacrus® at the same time as other preparations to be used on the skin or while taking oral corticosteroids (e.g. cortisone) or medicines which affect the immune system has not been studied.
Using Tacrus® with food and drink
While using Tacrus®, drinking alcohol may cause the skin or face to become flushed or red and feel hot.

Dosage and Administration

Always use Tacrus® exactly as your doctor has told you. You should check with your doctor or pharmacist if you are not sure.

- Apply Tacrus® as thin layer to affected areas of your skin.
- Tacrus® may be used on most parts of the body, including the face and the neck and in the creases of your elbows and knees.
- Avoid using the ointment inside your nose or mouth or in your eyes. If the ointment gets on any of these areas, it should be thoroughly wiped off and/or rinsed off with water. Do not cover the skin being treated with bandages or wraps.
- Wash your hands after applying Tacrus® unless your hands are also being treated. Before applying Tacrus® after a bath or shower, be sure your skin is completely dry.

Children (2 years of age and older):
Apply Tacrolimus 0.03% ointment twice a day for up to three weeks, once in the morning and once in the evening. Afterwards the ointment should be used once a day on each affected region of the skin until the eczema has gone away.

Adults (16 years of agc and older):
Two strengths of Tacrolimus (0.03% and 0.1% ointment) are available for adults patients (16 years of age and older). Your doctor will decide which strength is best for you.
Usually, treatment is started with Tacrus® 0.1% ointment twice a day, once in the morning and once in the evening, until the eczema has cleared. Depending on the response of your eczema your doctor will decide if the frequency of application can be reduced or the lower strength, Tacrolimus 0.03% ointment, can be used.
Treat each affected region of your skin until the eczema has gone away. Improvement is usually seen within one week. If you do not see any improvement after two weeks, see your doctor about other possible treatments. You may be told by your doctor to use Tacrus® 0.1% ointment twice weekly once your atopic dermatitis has cleared or almost cleared (Tacrolimus 0.03% for children and Tacrs® 0.1% for adults). Tacrus® 0.1% ointment should be applied once a day twice weekly (e.g. Monday and Thursday) to areas of your body commonly affected by atopic dermatitis. There should be 2-3 days without Tacrus® treatment between applications.

If symptoms reappear you should use Tacrus® twice daily as outlined above and arrange to see your doctor to review your treatment.

Possible Side Effects

Like all medicines, Tacrus® can cause side effects, although not everybody gets them.

Very common (probably affecting more than 1 in 10): burning sensation and itching; these symptoms are usually mild to moderate and generally go away within one week of using Tacrus®.

- Common (probably affecting up to 1 in 10): Redness, feeling of warmth, pain, increased skin sensitivity (especially to hot and cold) skin tingling, rash, local skin infection regardless of specific cause including but not limited to: inflamed or infected hair follicles,cold sores,generalized herpes simplex infections,facial flushing or skin irritation after drinking alcohol is also common.
- Uncommon (probably affecting less than 1 in 100): acne.

Following twice-weekly treatment application site infections have been reported in children and adults, impetigo, a superficial bacterial skin infection that usually produces blisters or sores on the skin,has been reported in children. Rosaceae (facial redness), Rosaceae- like dermatitis and oedema at the application site has been reported during post marketing experience.

Since commercial availability a very small number of people who have used Tacrolimus ointment have had malignancies (for example, skin and lymphoma). However a link to Tacrolimus ointment has not been confirmed or refuted on the available evidence so far.
If any of the side effects gets serious, or if you notice any side effect not listed in this leaflet, please tell your doctor or pharmacist.

Overdosage

If you accidentaly swallow some ointment
If you accidentally swallow the ointment, consult your doctor or pharmacist as soon as possible. Do not try to induce Vomiting.
If you forget to use Tacrus®

If you forget to apply the ointment at the scheduled time, do it as soon as you remember and then continue as before. If you have any further questions on the use of this product, ask your doctor or pharmacist.

How supplied

10 g packs.

30 g packs.

Storage

Do not store above 25 °C.
Keep out of the reach and sight of children.
Do not use Tacrus® after the expiry date which is stated on the tube and carton after Exp. The expiry date refers to the last day of that month.

THIS IS A MEDICAMENT

- Medicament is a product which affects your health and its consumption contrary to instructions is dangerous for you.
- Strictly follow the doctor's prescription, the method of use and the instruction of the pharmacist who sold the medicament.
- The doctor and the pharmacist are experts in medicine, its benefits and risks.
- Do not by yourself interrupt the period of treatment prescribed for you.
- Do not repeat the same prescription without consulting your doctor.
- Keep medicament out of reach of children.